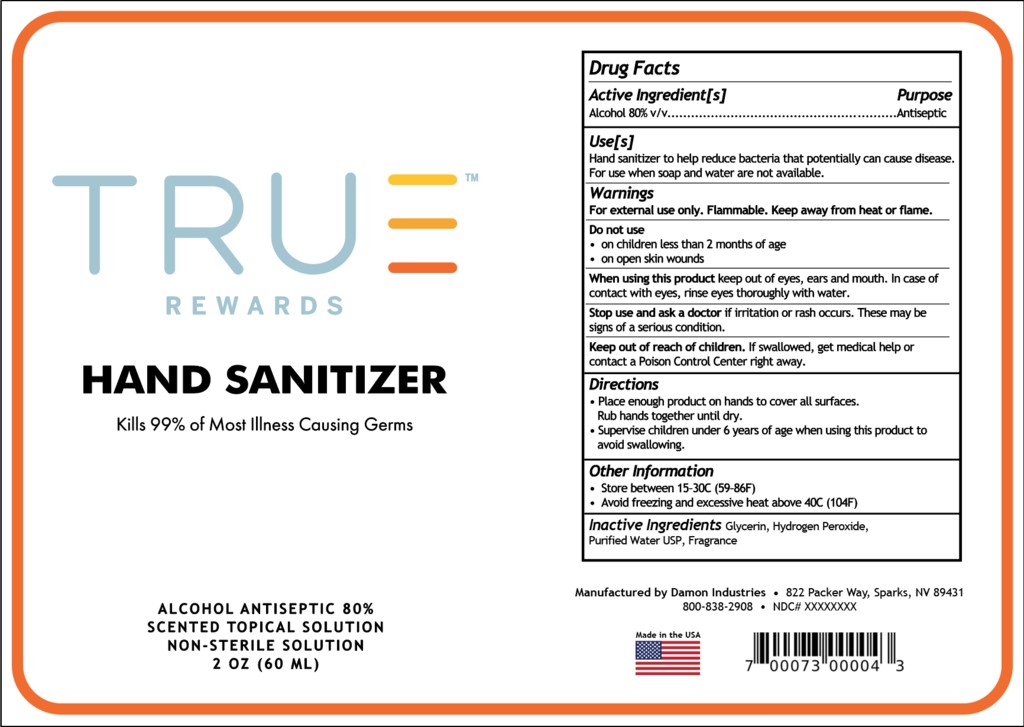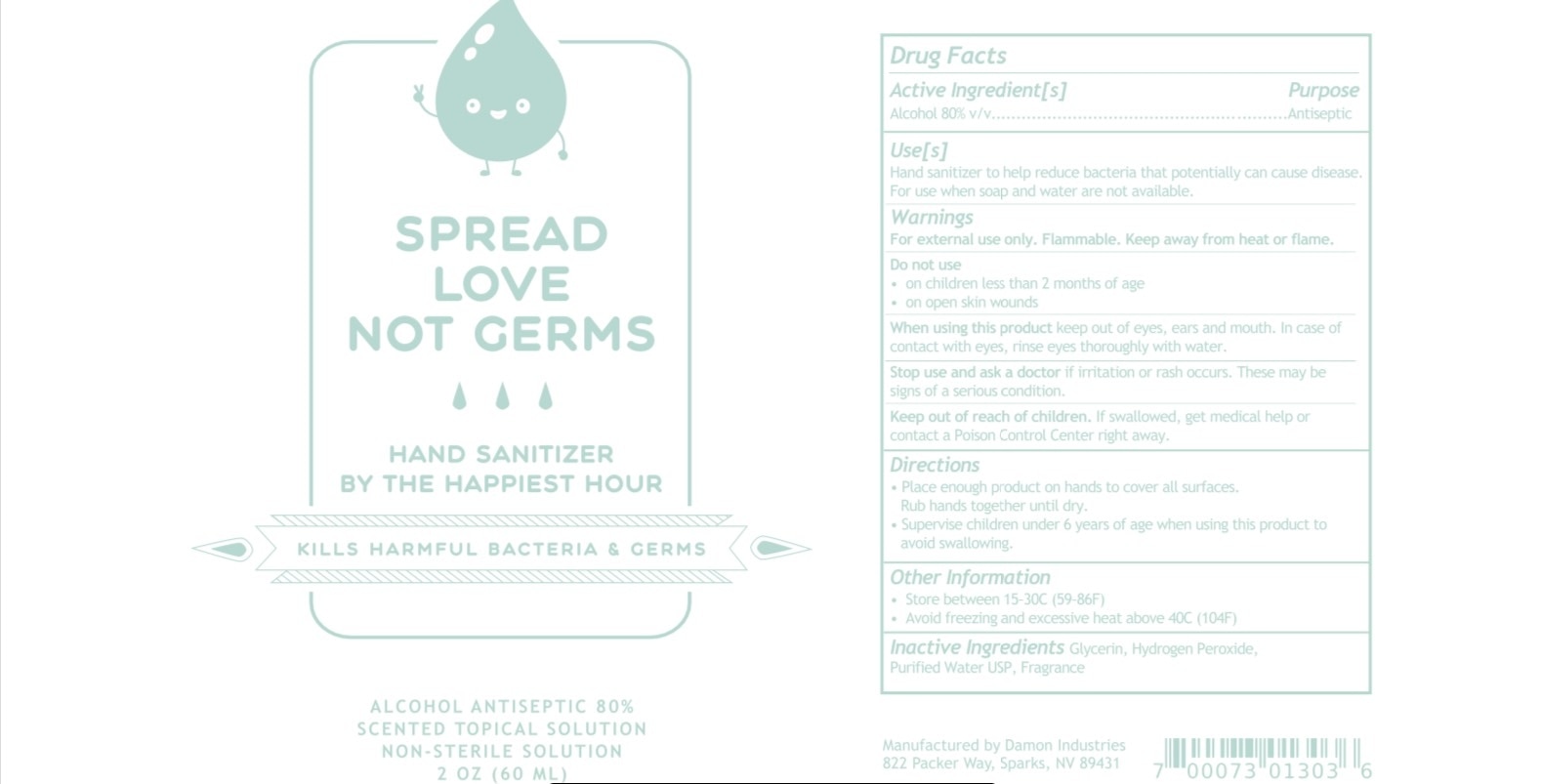 DRUG LABEL: Spread Love Not Germs
NDC: 74682-003 | Form: LIQUID
Manufacturer: Damon Industries
Category: otc | Type: HUMAN OTC DRUG LABEL
Date: 20200729

ACTIVE INGREDIENTS: ALCOHOL 80 mL/100 mL
INACTIVE INGREDIENTS: HYDROGEN PEROXIDE; WATER; LIMONENE, (+/-)-; DIHYDROMYRCENOL; METHYL DIHYDROJASMONATE (SYNTHETIC); 2-ACETOXY-1,8-CINEOLE, (+)-ENDO-; GLYCERIN

Active Ingredient(s)

Alcohol 80% v/v Purpose: Antiseptic

Purpose

Antiseptic Hand Sanitizer

Use(s)

Hand Sanitizer to help reduce bacteria that potentially can cause disease. For use when soap and water are not available

Warnings

For External use only. Flammable. Keep away from heat or flame.

Do not use

on children less than 2 months of age

on open skin wounds

When using this product keep out of eyes, ears and mouth. In case of contact with eyes, rinse eyes thoroughly with water.

Stop use and ask doctor if irritation or rash occurs. These may be signs of a serious condition.

Keep out of reach of children. If swallowed, get medical help or contact a Poison Control Center right away.

Directions

Place enough product on hands to cover all surfaces. Rub hands until dry.

Supervise children under 6 years of age when using this product to avoid swallowing.

Other Information

Store between 15-30C (59-86F)

Avoid freezing and excessive heat above 40C (104F)

Inactive Ingredients

Glycerin, Hydrogen Peroxide, Purified Water USP, Fragrance

Package Label - Principal Display Panel

60ml NDC: 74682-003-53

60ml 74682-004-53